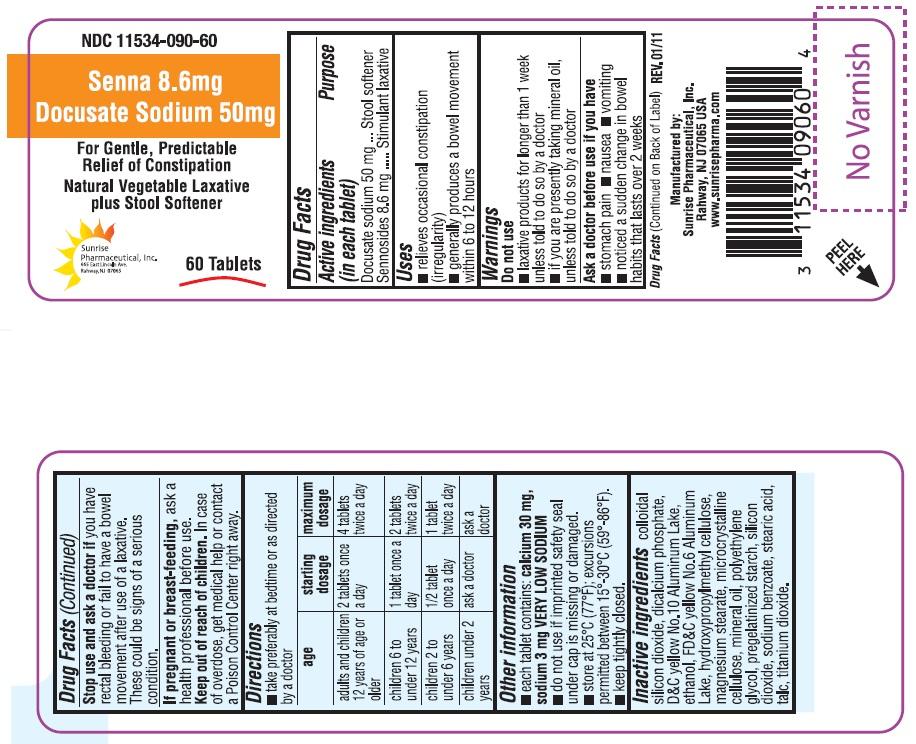 DRUG LABEL: Senna and Docusate Sodium
NDC: 11534-090 | Form: TABLET, FILM COATED
Manufacturer: Sunrise Pharmaceutical Inc
Category: otc | Type: HUMAN OTC DRUG LABEL
Date: 20130807

ACTIVE INGREDIENTS: DOCUSATE SODIUM 50 mg/1 1; SENNOSIDES 8.6 mg/1 1
INACTIVE INGREDIENTS: DIBASIC CALCIUM PHOSPHATE DIHYDRATE; SILICON DIOXIDE; FD&C YELLOW NO. 6; D&C YELLOW NO. 10; HYPROMELLOSE 2208 (100 MPA.S); MAGNESIUM STEARATE; CELLULOSE, MICROCRYSTALLINE; MINERAL OIL; POLYETHYLENE GLYCOLS; STARCH, CORN; SODIUM BENZOATE; STEARIC ACID; TITANIUM DIOXIDE; TALC; ALCOHOL

Unknown Title

OTC - ACTIVE INGREDIENT

Docusate sodium 50 mg

Sennosides 8.6 mg

OTC - PURPOSE

Stool softener and Stimulant laxative

INDICATIONS AND USAGE

- relieves occasional constipation (irregularity)
- generally produces a bowel movement within 6 to 12 hours

WARNINGS

Do not use:

- laxative products for longer than 1 week unless told to do so by a doctor
- if you are presently taking mineral oil, unless told to do so by a doctor

OTC - ASK A DOCTOR BEFORE USE IF YOU HAVE

- Stomach pain
- Nausea
- Vomiting
- Noticed a sudden change in bowel habits that lasts over 2 weeks

OTC - STOP USE AND ASK A DOCTOR IF

You have rectal bleeding or fail to have a bowel movement after use of a laxative. These could be signs of a serious condition.

OTC – IF PREGNANT OR BREAST FEEDING

Ask a health professional before use.

OTC - KEEP OUT OF REACH OF CHILDREN

In case of overdose, get medical help or contact a Poison Control Center right away.

DOSAGE AND ADMINISTRATION

- Take preferably at bedtime or as directed by a doctor

age | starting dosage | maximum dosage
adults and children 12 years of age or older | 2 tablets once a day | 4 tablets twice a day
children 6 to under 12 years | 1 tablet once a day | 2 tablets twice a day
children 2 to under 6 years | ½ tablet once a day | 1 tablet twice a day
children under 2 years | ask a doctor | ask a doctor

OTHER INFORMATION

- Each tablet contains: calcium 30 mg, sodium 3 mg VERY LOW SODIUM
- Do not use if imprinted safety seal under cap is missing or damaged.
- Store at 25° C (77° F); excursions permitted between 15° C-30° C (59° -86° F).
- Keep tightly closed.

INACTIVE INGREDIENT

Colloidal silicon dioxide, dicalcium phosphate, D&C yellow No 10 Aluminum Lake, ethanol, FD&C yellow No 6 Aluminum Lake, hydroxypropyl methyl cellulose, magnesium stearate, microcrystalline cellulose, mineral oil, polyethylene glycol, pregelatinized starch, silicon dioxide, sodium benzoate, stearic acid, talc, titanium dioxide